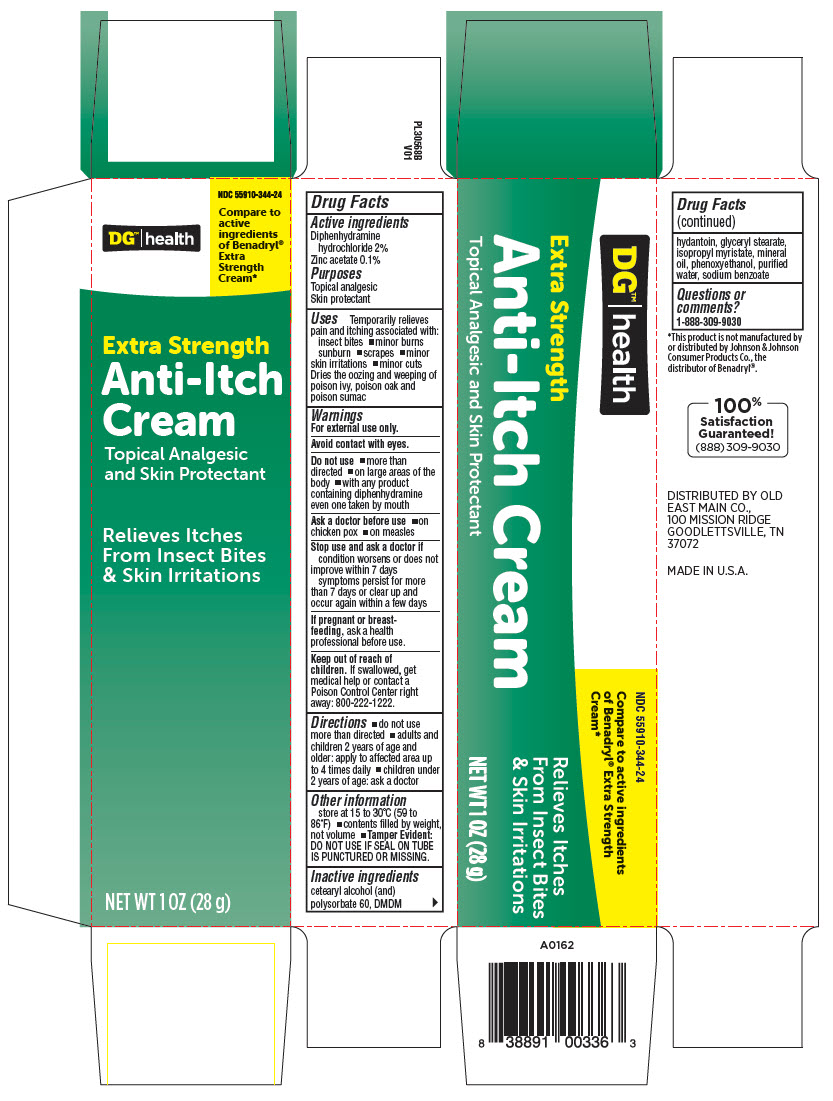 DRUG LABEL: DG Anti-Itch
NDC: 55910-344 | Form: CREAM
Manufacturer: Dollar General
Category: otc | Type: HUMAN OTC DRUG LABEL
Date: 20241217

ACTIVE INGREDIENTS: Diphenhydramine hydrochloride 20 mg/1 g; Zinc acetate 0.1 mg/1 g
INACTIVE INGREDIENTS: CETOSTEARYL ALCOHOL; polysorbate 60; DMDM HYDANTOIN; GLYCERYL MONOSTEARATE; ISOPROPYL MYRISTATE; PHENOXYETHANOL; mineral oil; Sodium Benzoate; WATER

DG™ Anti-Itch
Anti-Itch Cream

Drug Facts

ACTIVE INGREDIENT

PURPOSE

Active ingredients | Purposes
Diphenhydramine hydrochloride 2% | Topical analgesic
Zinc acetate 0.1% | Skin protectant

Uses

Temporarily relieves pain and itching associated with:

- insect bites
- minor burns
- sunburn
- scrapes
- minor skin irritations
- minor cuts

Dries the oozing and weeping of poison ivy, poison oak and poison sumac

Warnings

For external use only.

Avoid contact with eyes.

Do Not Use

- more than directed
- on large areas of the body
- with any product containing diphenhydramine even one taken by mouth

Ask a doctor before use

- on chicken pox
- on measles

Stop use and ask a doctor if

- condition worsens or does not improve within 7 days
- symptoms persist for more than 7 days or clear up and occur again within a few days

PREGNANCY OR BREAST FEEDING

If pregnant or breast-feeding, ask a health professional before use.

Keep out of reach of children. If swallowed, get medical help or contact a Poison Control Center right away: 800-222-1222.

Directions

- do not use more than directed
- adults and children 2 years of age and older: apply to affected area up to 4 times daily
- children under 2 years of age: ask a doctor

Other information

- store at 15 to 30°C (59 to 86°F)
- contents filled by weight, not volume
- Tamper Evident: DO NOT USE IF SEAL ON TUBE IS PUNCTURED OR MISSING.

Inactive ingredients

cetearyl alcohol (and) polysorbate 60, DMDM hydantoin, glyceryl stearate, isopropyl myristate, mineral oil, phenoxy ethenol, purified water, sodium benzoate

Questions or comments?

1-888-309-9030

DISTRIBUTED BY OLD
EAST MAIN CO.,
100 MISSION RIDGE
GOODLETTSVILLE, TN
37072

PRINCIPAL DISPLAY PANEL - 28 g Tube Carton

DG™|health

NDC 55910-344-24

Compare to
active
ingredients
of Benadryl®
Extra
Strength
Cream*

Extra Strength
Anti-Itch
Cream
Topical Analgesic
and Skin Protectant

Relieves Itches
From Insect Bites
& Skin Irritations

NET WT 1 OZ (28 g)